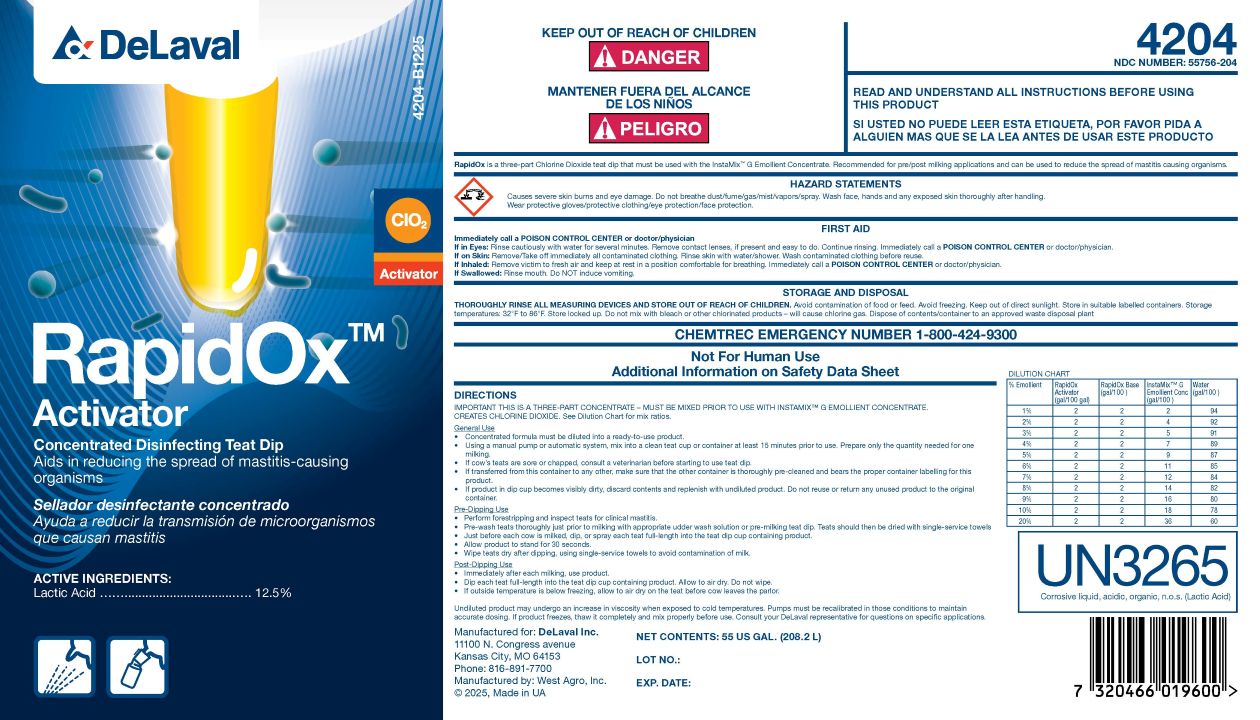 DRUG LABEL: RapidOx Activator
NDC: 55756-204 | Form: SOLUTION, CONCENTRATE
Manufacturer: DeLaval
Category: animal | Type: OTC ANIMAL DRUG LABEL
Date: 20260125

ACTIVE INGREDIENTS: LACTIC ACID 125 g/1 L
INACTIVE INGREDIENTS: C9-11 PARETH-8; WATER

RapidOx™ Activator

PURPOSE

Concentrated Disinfecting Teat Dip

Aids in reducing the spread of mastitis-causing organisms

ACTIVE INGREDIENTS:

Lactic Acid ................................. 12.5%

KEEP OUT OF REACH OF CHILDREN

! DANGER

PRECAUTIONS

READ AND UNDERSTAND ALL INSTRUCTIONS BEFORE USING THIS PRODUCT

DESCRIPTION

RapidOx is a three-part Chlorine Dioxide teat dip that must be used with the InstaMix G Emollient Concentrate. Recommended for pre/post milking applications and can be used to reduce the spread of mastitis causing organisms.

WARNINGS

HAZARD STATEMENTS

Causes severe skin burns and eye damage. Do not breathe dust/fume/gas/mist/vapors/spray. Wash face, hands and any exposed skin thoroughly after handling. Wear protective gloves/protective clothing/eye protection/face protection.

UN3265

Corrosive liquid, acidic, organic, n.o.s.(Lactic Acid)

FIRST AID

Immediately call a POISON CENTER or doctor/physician

If in Eyes: Rinse cautiously with water for several minutes. Remove contact lenses, if present and easy to do. Continue rinsing. Immediately call a POISON CENTER or doctor/physician.

If on Skin: Remove/Take off immediately all contaminated clothing. Rinse skin with water/shower. Wash contaminated clothing before reuse.

If Inhaled: Remove victim to fresh air and keep at rest in a position comfortable for breathing. Immediately call a POISON CENTER or doctor/physician.

If Swallowed: Rinse mouth. Do NOT induce vomiting.

STORAGE AND DISPOSAL

THOROUGHLY RINSE ALL MEASURING DEVICES AND STORE OUT OF REACH OF CHILDREN. Avoid contamination of food or feed. Avoid freezing. Keep out of direct sunlight. Store in suitable labelled containers. Storage temperatures: 32°F to 86°F. Store locked up. Do not mix with bleach or other chlorinated products - will cause chlorine gas. Dispose of contents/container to an approved waste disposal plant.

PRECAUTIONS

CHEMTREC EMERGENCY NUMBER 1-800-424-9300

Not for Human Use

Additional Information on Safety Data Sheet

DIRECTIONS

IMPORTANT THIS IS A THREE-PART CONCENTRATE - MUST BE MIXED PRIOR TO USE WITH INSTAMIX™ G EMOLLIENT CONCENTRATE.

CREATES CHLORINE DIOXIDE See Dilution Chart for mix ratios.

General Use

- Concentrated formula must be diluted into a ready-to-use product.
- Using a manual pump or automatic system, mix into a clean teat cup or contaner at least 15 minutes prior to use. Prepare only the quantity needed for one milking.
- If cow's teats are sore or chapped, consult a veterinarian before starting to use teat dip.
- If transferred from this contain to any other, make sure that the other container is thoroughly pre-cleaned and bears the proper container labeling for this product.
- If product in dip cup becomes visibly dirty, discard contents and replenish with undiluted product. Do not reuse or return any unused product to the original container.

Pre-Dipping Use

- Perform forestripping and inspect teats for clinical mastitis.
- Pre-wash teats thoroughly just prior to milking with appropriate udder wash solution or pre-milking teat dip. Teats should then be dried with single-service towels.
- Just before each cow is milked, dip, or spray each teat full-length into the teat dip cup containing product.
- Allow product to stand for 30 seconds.
- Wipe teats dry after dipping, using single-service towels to avoid contamination of milk

Post-Dipping Use

- Immediately after each milking, use product.
- Dip each teat full-length into the teat dip cup containing product. Allow to air dry. Do not wipe.
- If outside temperature is below freezing, allow to air dry on the teat before cow leaves the parlor.

Undiluted product may undergo an increase in viscosity when exposed to cold temperatures. Pumps must be recalibrated in those conditions to maintain accurate dosing. If product freezes, thaw it completely and mix properly before use. Consult your DeLaval representative for questions on specific applications.

DILUTION CHART
% Emollient | RapidOx Activator (gal/100) | RapidOx Base (gal/100) | Instamix™ G Emollient Conc (gal/100) | Water (gal/100)
1% | 2 | 2 | 2 | 94
2% | 2 | 2 | 4 | 92
3% | 2 | 2 | 5 | 91
4% | 2 | 2 | 7 | 89
5% | 2 | 2 | 9 | 87
6% | 2 | 2 | 11 | 85
7% | 2 | 2 | 12 | 84
8% | 2 | 2 | 14 | 82
9% | 2 | 2 | 16 | 80
10% | 2 | 2 | 18 | 78
20% | 2 | 2 | 36 | 60

Manufactured for: DeLaval Inc.

11100 N. Congress Avenue

Kansas City, MO 6153

Phone: 816-891-7700

Manufactured by: West Agro, Inc.

© 2025, Made in UA